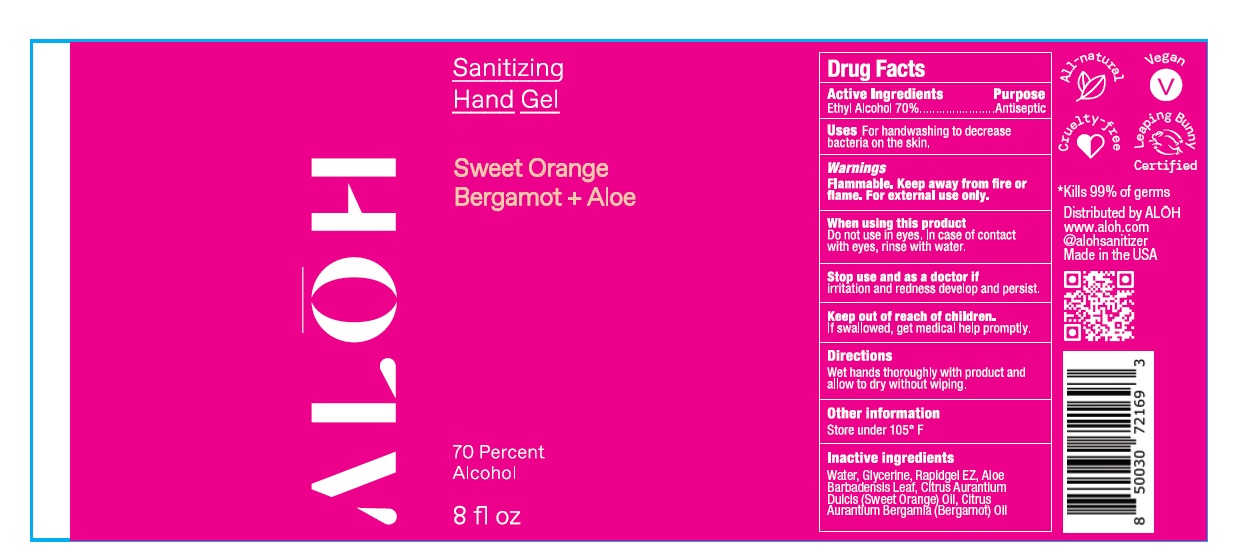 DRUG LABEL: Sweet Orange Bergamot and Aloe
NDC: 82355-002 | Form: GEL
Manufacturer: ALO New York LLC
Category: otc | Type: HUMAN OTC DRUG LABEL
Date: 20250618

ACTIVE INGREDIENTS: ALCOHOL 70 mL/100 mL
INACTIVE INGREDIENTS: GLYCERIN; WATER; RAPIDGEL EZ1; ALOE BARBADENSIS LEAF; ORANGE OIL, COLD PRESSED; CITRUS AURANTIUM BERGAMIA (BERGAMOT) LEAF OIL

ALO Brands

Active ingredients

Ethyl Alcohol

Purpose

Antiseptic

Uses

For handwashing to decrease bacteria on the skin

Warnings

Flammable. Keep away from fire or flame. For external use only.

When using this product

Do not use in eyes. In case of contact with eyes, rinse with water.

Stop use and ask doctor if

irritation and redness develop and persist.

Keep out of reach of chidren.

If swallowed, get medical help promptly.

Directions

Wet hands thoroughly with product and allow to dry without wiping.

Other information

Store under 105°F

Inactive Ingredients

Water, Glycerine, Rapidgel EZ, Aloe Barbadensis Leaf, Citrus Aurantium Dulcis (Sweet Orange) Oil, Citrus Aurantium Bergamia (Bergamot)Oil

PACKAGE LABEL

NDC 82355-002-08

ALOH Sanitizing Hand Gel

Sweet Orange Bergamot + Aloe

70 Percent Alcohol

8 fl oz